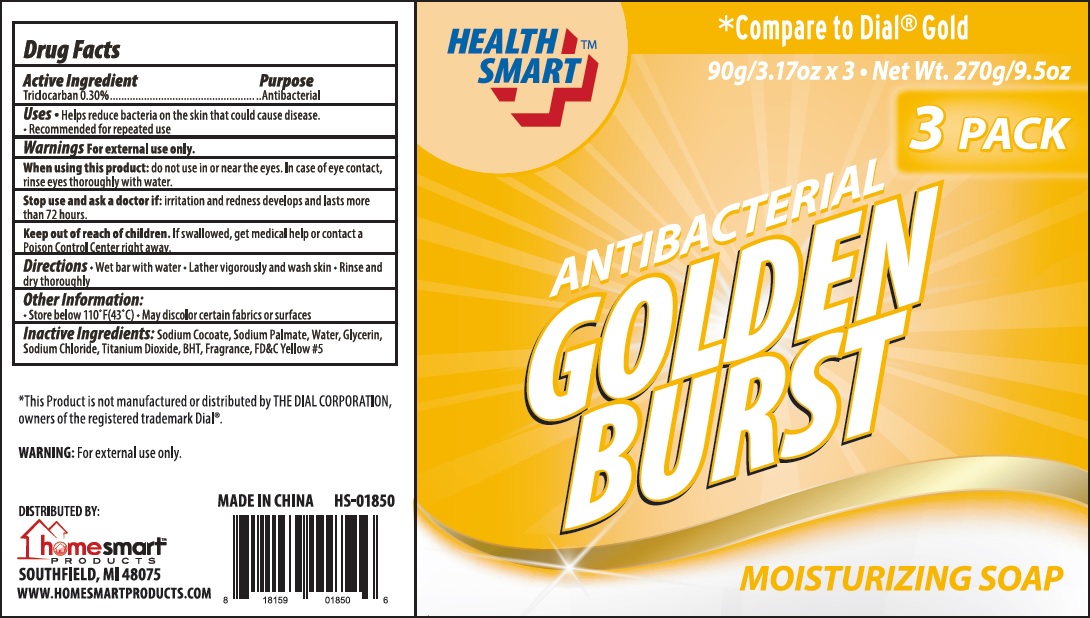 DRUG LABEL: Antibacterial Golden Burst
NDC: 52862-120 | Form: SOAP
Manufacturer: International Wholesale, Inc.
Category: otc | Type: HUMAN OTC DRUG LABEL
Date: 20150715

ACTIVE INGREDIENTS: TRICLOCARBAN 0.3 g/100 g
INACTIVE INGREDIENTS: SODIUM COCOATE; SODIUM PALMATE; WATER; GLYCERIN; SODIUM CHLORIDE; TITANIUM DIOXIDE; BUTYLATED HYDROXYTOLUENE; FD&C YELLOW NO. 5

Active Ingredient

Triclocarban 0.30%

Purpose

Antibacterial

Uses

- Helps reduce bacteria on the skin that could cause disease.
- Recommended for repeated use

Warnings

For external use only

When using this product:

do not use in or near the eyes. In case of eye contact, rinse eyes thoroughly with water.

Stop use and ask a doctor if:

irritation and redness develops and lasts more than 72 hours.

Keeps out of reach of children.

If swallowed, get medical help or contact a Poison Control Center right away.

Directions

- Wet bar with water
- Lather vigorously and wash skin
- Rinse and dry thoroughly

Other Information

- Store below 110° F (43° C)
- May discolor certain fabrics or surfaces

Inactive Ingredients

Sodium Cocoate, Sodium Palmate, Water, Glycerin, Sodium Chloride, Titanium Dioxide, BHT, Fragrance, FD&C Yellow #5